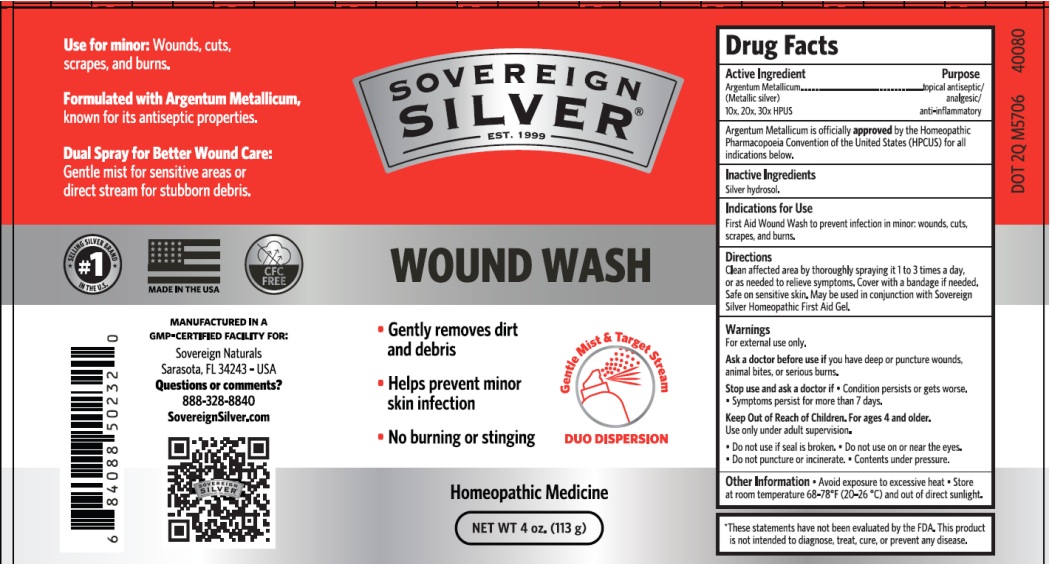 DRUG LABEL: SOVEREIGN SILVER HOMEOPATHIC WOUND WASH
NDC: 52166-022 | Form: LIQUID
Manufacturer: Natural Immunogenics Corp.dba SOVEREIGN NATURALS
Category: homeopathic | Type: HUMAN OTC DRUG LABEL
Date: 20250618

ACTIVE INGREDIENTS: SILVER 30 [hp_X]/1 g
INACTIVE INGREDIENTS: WATER

Active Ingredient

ARGENTUM METALLICUM 10X, 20X, 30X HPUS

Purpose

TOPICAL ANTISEPTIC / ANALGESIC / ANTI-INFLAMMATORY

Uses

FIRST AID WOUND WASH TO PREVENT INFECTION IN MINOR: WOUNDS, CUTS, SCRAPES AND BURNS. GENTLY REMOVES DIRT AND DEBRIS; HELPS PREVENT MINOR SKIN INFECTION

Warnings

- For external use only.
- Ask a doctor before use ifyou have deep or puncture wounds, animal bites, or serious burns.
- Stop use and ask a doctor if. Condition persists or gets worse.
- Symptoms persist for more than 7 days.
- Keep Out of Reach of Children. For ages 4 and older. Use only under adult supervision.
- Do not use if seal is broken.. Do not use on or near the eyes.
- Do not puncture or incinerate. Contents under pressure.

Directions

Clean affected area by thoroughly spraying it 1 to 3 times a day, oras needed to relieve symptoms, Cover with a bandage if needed.
Safe on sensitive skin. May be used in conjunction with Sovereign Silver Homeopathic First Aid Gel.

Inactive Ingredients

Water, silver hydrosol